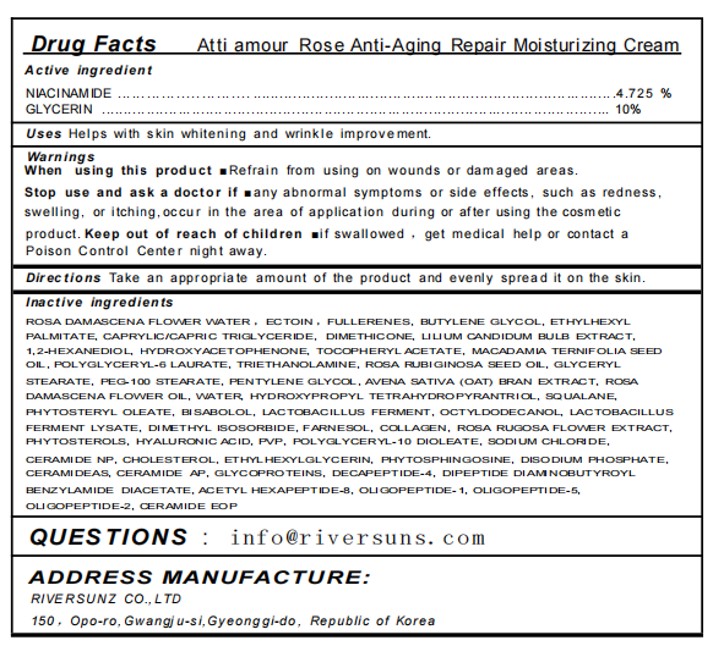 DRUG LABEL: Atti amour Rose Anti-Aging Repair Moisturizing Cream
NDC: 84601-004 | Form: CREAM
Manufacturer: RIVER SUNZ co.,Ltd
Category: otc | Type: HUMAN OTC DRUG LABEL
Date: 20251106

ACTIVE INGREDIENTS: GLYCERIN 10 g/100 g; NIACINAMIDE 4.725 g/100 g
INACTIVE INGREDIENTS: PEG-100 STEARATE; SODIUM PHOSPHATE, DIBASIC, ANHYDROUS; DIMETHICONE; CERAMIDE 4; COLLAGEN, SOLUBLE, FISH SKIN; ECTOINE; ETHYLHEXYL PALMITATE; MEDIUM-CHAIN TRIGLYCERIDES; HYALURONIC ACID; ROSA DAMASCENA FLOWER OIL; PENTYLENE GLYCOL; HYDROXYPROPYL TETRAHYDROPYRANTRIOL; ALLANTOIN; PHYTOSPHINGOSINE; ACETYL HEXAPEPTIDE-8; TROLAMINE; LEVOMENOL; FARNESOL; CERAMIDE NP; 1,2-HEXANEDIOL; MACADAMIA OIL; DIPEPTIDE DIAMINOBUTYROYL BENZYLAMIDE DIACETATE; STIGMASTERYL OLEATE; LILIUM CANDIDUM BULB; BUTYLENE GLYCOL; CERAMIDE AP; SQUALANE; ROSA RUBIGINOSA SEED OIL; DIMETHICONE/VINYL DIMETHICONE CROSSPOLYMER (HARD PARTICLE); OCTYLDODECANOL; LACTOBACILLUS REUTERI F275 STRAIN; ROSA RUGOSA FLOWER; CERAMIDE EOS; ETHYLHEXYLGLYCERIN; ALPHA-TOCOPHEROL ACETATE; DIMETHYL ISOSORBIDE; WATER; POLYGLYCERYL-6 LAURATE; HYDROLYZED WHEAT PROTEIN (ENZYMATIC, 3000 MW); BUCKMINSTERFULLERENE; HYDROXYACETOPHENONE; OAT BRAN; POLYGLYCERYL-10 DIOLEATE; CHOLESTEROL; POVIDONE; GLYCERYL MONOSTEARATE; SODIUM CHLORIDE

84601-004 Atti amour Rose Anti-Aging Repair Moisturizing Cream

ACTIVE INGREDIENT

NIACINAMIDE 4.725%
GLYCERIN 10%

PURPOSE

Helps with skin whitening and wrinkle improve ment.

Keep out of reach of children mif swallowed , get medical help or contact a Poison Control center night away.

INDICATIONS AND USAGE

Uses Helps with skin whitening and wrinkle improve ment.

When using this product Refrain from using on wounds or damaged areas.Stop use and ask a doctor if many abnormal symptoms or side effects, such as redness.swelling, or itching,occur in the area of application during or after using the cosmeticproduct. Keep out of reach of children if swallowed , get medical help or contact a Poison Control Center night away.

DOSAGE AND ADMINISTRATION

Take an appropriate amount of ointment and apply it evenly to the desired area

INACTIVE INGREDIENT

FULLERENES
ECTOIN
ROSA DAMASCENA FLOWER WATER
HYDROXYACETOPHENONE
1,2-HEXANEDIOL
LILIUM CANDIDUM BULB EXTRACT
MACADAMIA TERNIFOLIA SEED OIL
ETHYLHEXYL PALMITATE
BUTYLENE GLYCOL
CAPRYLIC/CAPRIC TRIGLYCERIDE
DIMETHICONE
POLYGLYCERYL-6 LAURATE
TOCOPHERYL ACETATE
TRIETHANOLAMINE
ROSA RUBIGINOSA SEED OIL
ROSA DAMASCENA FLOWER OIL
BISABOLOL
FARNESOL
PENTYLENE GLYCOL
AVENA SATIVA (OAT) BRAN EXTRACT
HYDROXYPROPYL TETRAHYDROPYRANTRIOL
OLIGOPEPTIDE-1
OLIGOPEPTIDE-5
OLIGOPEPTIDE-2
LACTOBACILLUS FERMENT
LACTOBACILLUS FERMENT LYSATE
ROSA RUGOSA FLOWER EXTRACT
COLLAGEN
HYALURONIC ACID
DECAPEPTIDE-4
GLYCOPROTEINS
DIPEPTIDE DIAMINOBUTYROYL BENZYLAMIDE DIACETATE
ACETYL HEXAPEPTIDE-8
DIMETHYL ISOSORBIDE
CERAMIDE EOP
CERAMIDE NP
CERAMIDE AS
CERAMIDE AP
PHYTOSPHINGOSINE
CHOLESTEROL
SQUALANE
PHYTOSTEROLS
PHYTOSTERYL OLEATE
PVP
GLYCERYL STEARATE
PEG-100 STEARATE
DISODIUM PHOSPHATE
SODIUM CHLORIDE
ETHYLHEXYLGLYCERIN
OCTYLDODECANOL
WATER
POLYGLYCERYL-10 DIOLEATE